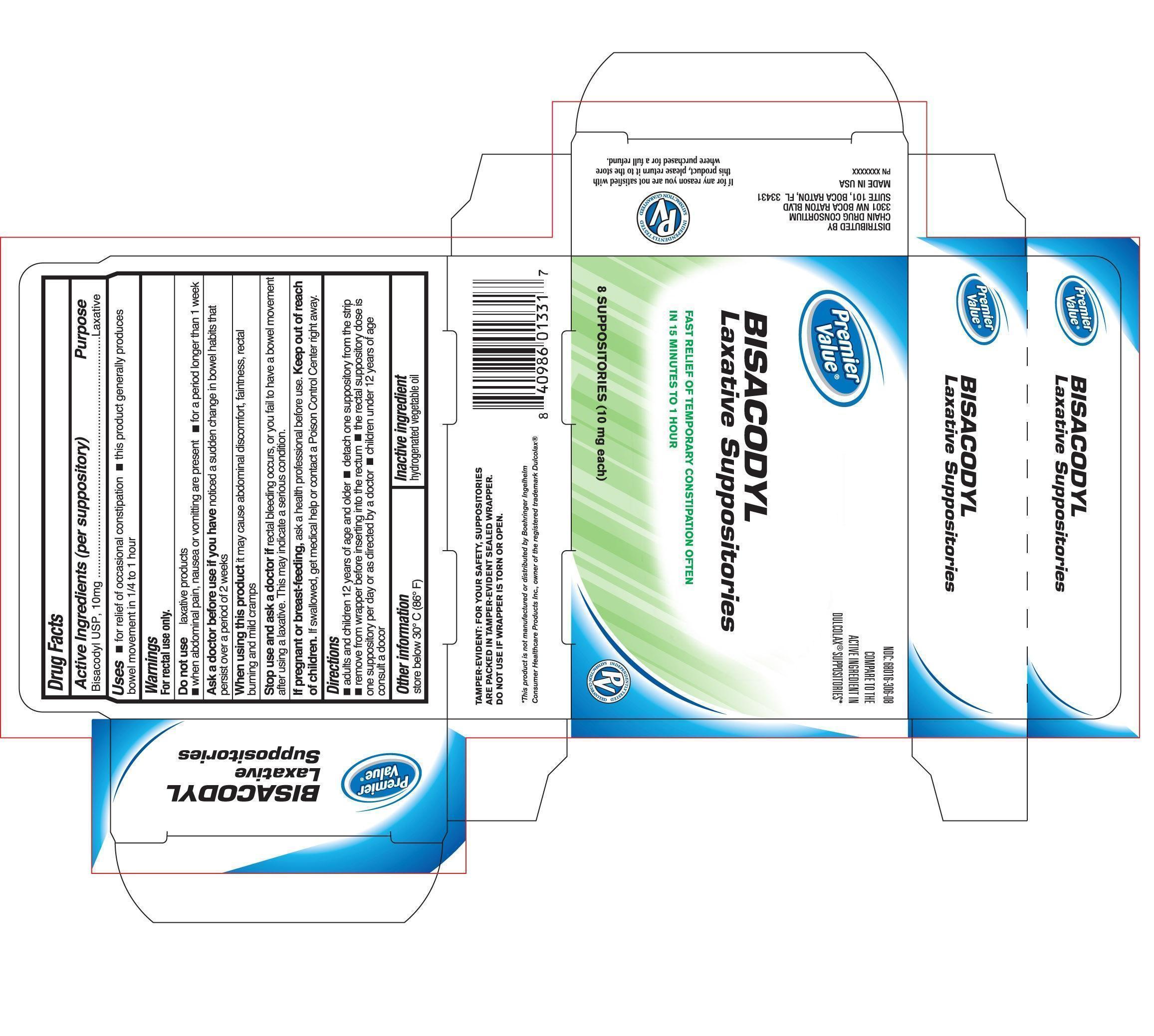 DRUG LABEL: Premier Value Bisacodyl Laxative
NDC: 68016-306 | Form: SUPPOSITORY
Manufacturer: Chain Drug Consortium
Category: otc | Type: HUMAN OTC DRUG LABEL
Date: 20150325

ACTIVE INGREDIENTS: BISACODYL 10 mg/2000 mg
INACTIVE INGREDIENTS: PALM KERNEL OIL 1990 mg/2000 mg

Active Ingredient (in each Suppository) Purpose

Bisacodyl USP, 10 mg.................................Laxative

Uses

Uses - For relief of occasional constipation -this product generally produces bowel movement in 1/4 hour to 1 hour

Warnings

For rectal use only.

Do not use laxative products

-when abdominal pain, nausea, or vomiting are present - for a period longer than 1 week

Ask a doctor before use if you have noticed a sudden change in bowel movement

burning and mild cramps

When using this product it may cause abdominal discomfort, faintness, rectal burning, and mild cramps

Stop use and ask a doctor if rectal bleeding occurs, or you fail to have bowel movement after using a laxative. This may indicate a serious condition.

If pregnant or breast-feeding, ask a health professional before use.

Keep out of reach of children. If swallowed, get medical help or contact a Poison Control Center right away.

Directions

-adults and children 12 years of age and older - detach one suppository from the strip

-remove from wrapper before inserting into the rectum - the rectal suppository dose is one suppository per day or as directed by a doctor - children under 12 years of age consult a doctor.

Other information

store below 30oC (86oF)

Inactive ingredient

hydrogenated vegetable oil

Purpose

Active Ingredient (in each Suppository) Purpose
Bisacodyl USP, 10 mg.................................Laxative